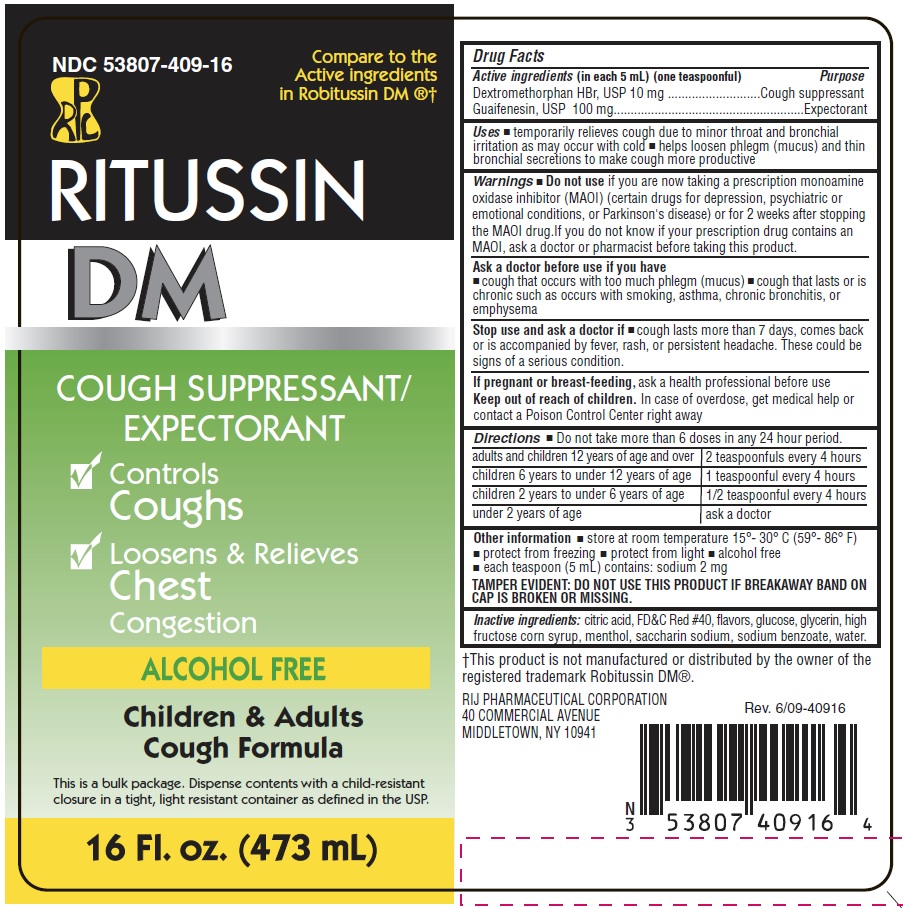 DRUG LABEL: Ritussin DM
NDC: 53807-409 | Form: LIQUID
Manufacturer: Rij Pharmaceutical Corporation
Category: otc | Type: HUMAN OTC DRUG LABEL
Date: 20180430

ACTIVE INGREDIENTS: DEXTROMETHORPHAN HYDROBROMIDE 10 mg/5 mL; GUAIFENESIN 100 mg/5 mL
INACTIVE INGREDIENTS: ANHYDROUS CITRIC ACID; DEXTROSE; FD&C RED NO. 40; HIGH FRUCTOSE CORN SYRUP; MENTHOL; SACCHARIN SODIUM; SODIUM BENZOATE; WATER; GLYCERIN

Drug Facts

Active ingredients (in each 5 mL)(one teaspoonful)

Dextromethorphan HBr, USP 10 mg

Guaifenesin, USP 100 mg

Purpose

Cough suppressant

Expectorant

Use

temporarily relieves cough due to minor throat and bronchial irritation as may occur with cold

helps loosen phlegm (mucus) and thin bronchial secretions to make coughs more productive

Warnings

Do not use

- if you are now taking a prescription monoamine oxidase inhibitor (MAOI) (certain drugs for depression, psychiatric, or emotional conditions, or Parkinson's disease), or for 2 weeks after stopping the MAOI drug. If you do not know if your prescription drug contains an MAOI, ask a doctor or pharmacist before taking this product.

Ask a doctor before use if you have

- cough that occurs with too much phlegm (mucus)
- cough that lasts or is chronic such as occurs with smoking, asthma, chronic bronchitis, or emphysema

Stop use and ask a doctor if cough lasts more than 7 days, comes back, or is accompanied by fever, rash, or persistent headache. These could be signs of a serious condition.

PREGNANCY OR BREAST FEEDING

If pregnant or breast-feeding, ask a health professional before use.

Keep out of reach of children. In case of overdose, get medical help or contact a Poison Control Center right away.

Directions

- do not take more than 6 doses in any 24-hour period

age | dose
adults and children 12 years of age and over | 2 teaspoonfuls every 4 hours
children 6 years to under 12 years of age | 1 teaspoonful every 4 hours
children 2 years to under 6 years of age | 1/2 teaspoonful every 4 hours
under 2 years of age | ask a doctor

Other information

- store at room temperature 15º - 30ºC (59º - 86ºF)
- protect from freezing.
- protect from light.
- Each teaspoon (5 mL) contains: sodium 2 mg.
- TAMPER EVIDENT: DO NOT USE THIS PRODUCT IF BREAKAWAY BAND ON CAP IS BROKEN OR MISSING

Inactive ingredients

citric acid, FD&C Red #40, flavors, glucose, glycerin, high fructose corn syrup, menthol, saccharin sodium, sodium benzoate, water